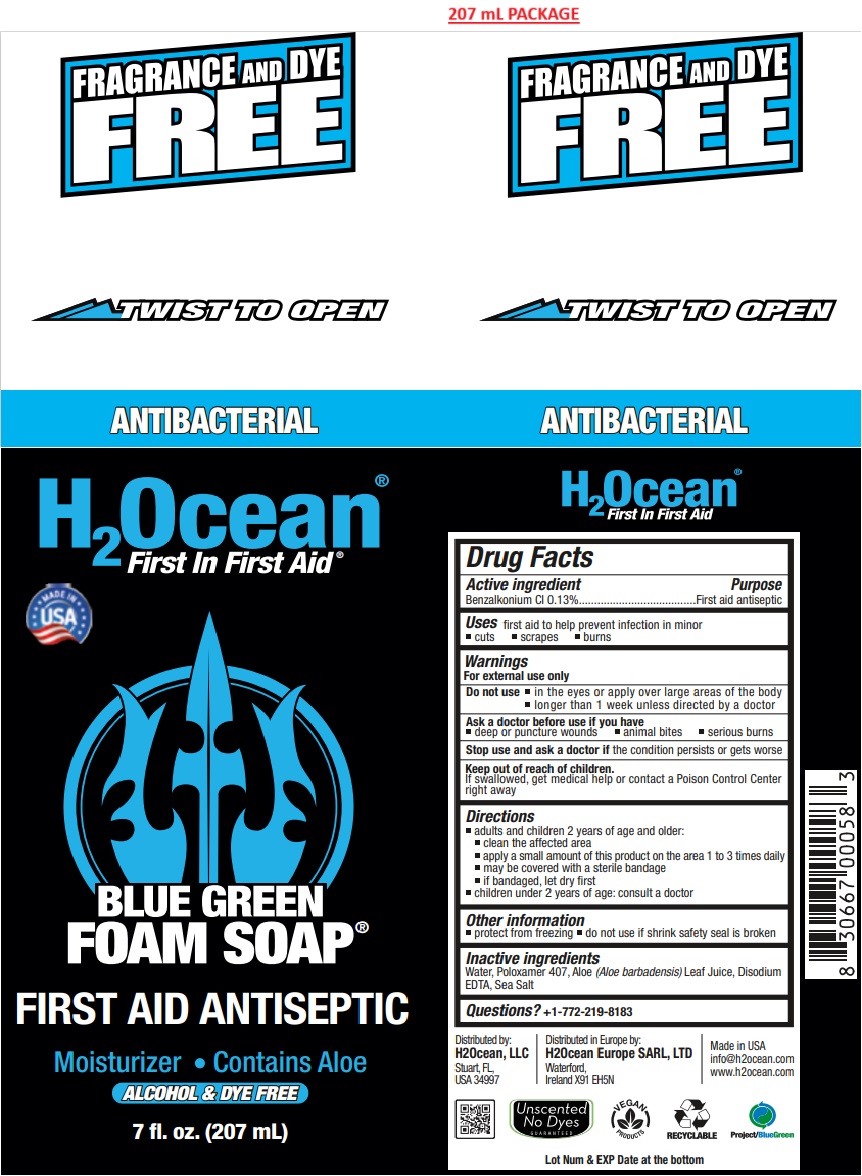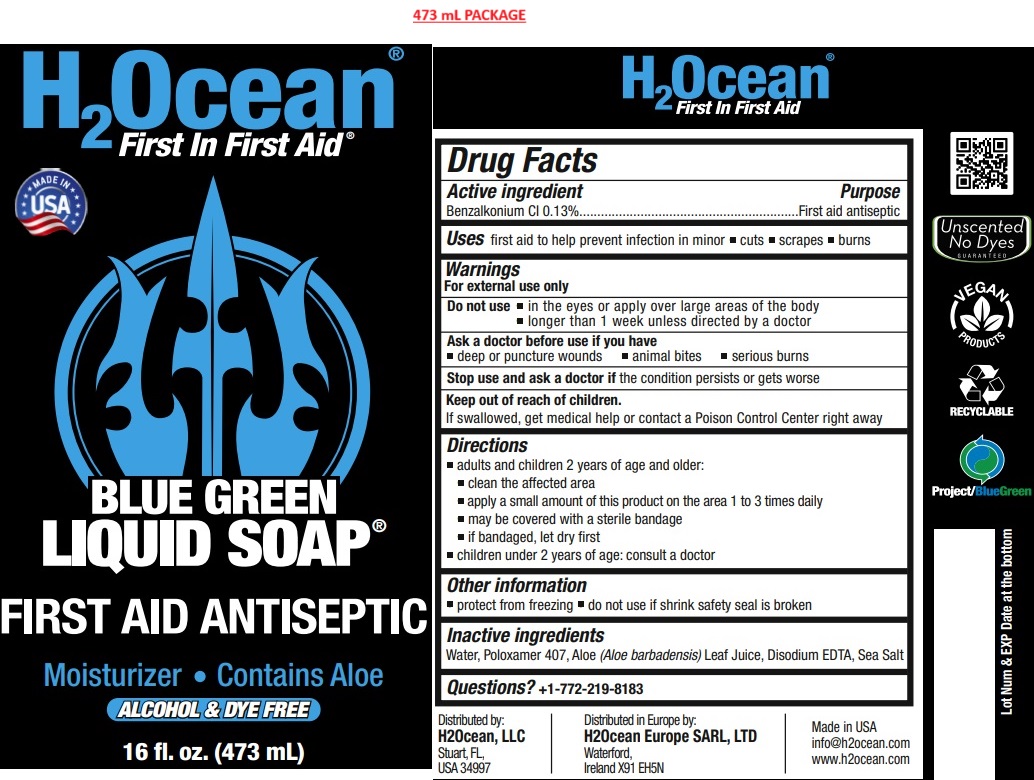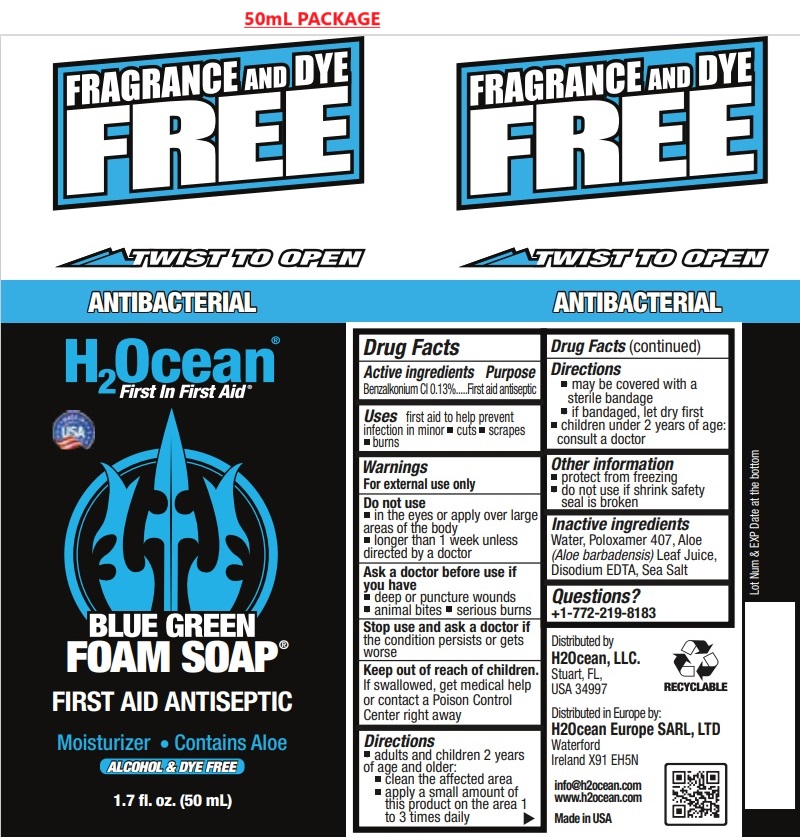 DRUG LABEL: Blue Green Foam
NDC: 70411-100 | Form: LIQUID
Manufacturer: H2Ocean, LLC
Category: otc | Type: HUMAN OTC DRUG LABEL
Date: 20241023

ACTIVE INGREDIENTS: BENZALKONIUM CHLORIDE 0.13 g/100 mL
INACTIVE INGREDIENTS: WATER; POLOXAMER 407; ALOE VERA LEAF; EDETATE DISODIUM; SEA SALT

BLUE GREEN FOAM

Active ingredient

Benzalkonium Cl 0.13%

Purpose

First aid antiseptic

Uses

first aid to help prevent infection in minor • cuts • scrapes • burns

Warnings

For external use only

Do not use • in the eyes or apply over large areas of the body
• longer than 1 week unless directed by a doctor

Ask a doctor before use if you have • deep or puncture wounds • animal bites • serious burns

Stop use and ask a doctor if the condition persists or gets worse

Keep out of reach of children. If swallowed, get medical help or contact a Poison Control Center right away

Directions

• adults and children 2 years of age and older:
• clean the affected area
• apply a small amount of this product on the area 1 to 3 times daily
• may be covered with a sterile bandage
• if bandaged, let dry first
• children under 2 years of age: consult a doctor

Other information

• protect from freezing • do not use if shrink safety seal is broken

Inactive ingredients

Water, Poloxamer 407, Aloe (Aloe barbadensis) Leaf Juice, Disodium EDTA, Sea Salt

Questions?

+1-772-219-8183

BLUE GREEN FOAM SOAP®

FIRST AID ANTISEPTIC

Moisturizer • Contains Aloe

ALCOHOL & DYE FREE

Distributed by:

H2Ocean, LLC
Stuart, FL,
USA 34997

Distributed in Europe by:
H2Ocean Europe SARL, LTD
Waterford,
Ireland X91 EH5N

Made in USA

info@h2ocean.com
www.h2ocean.com

Unscented No Dyes GUARANTEED

VEGAN PRODUCTS

RECYCLABLE

Project/BlueGreen